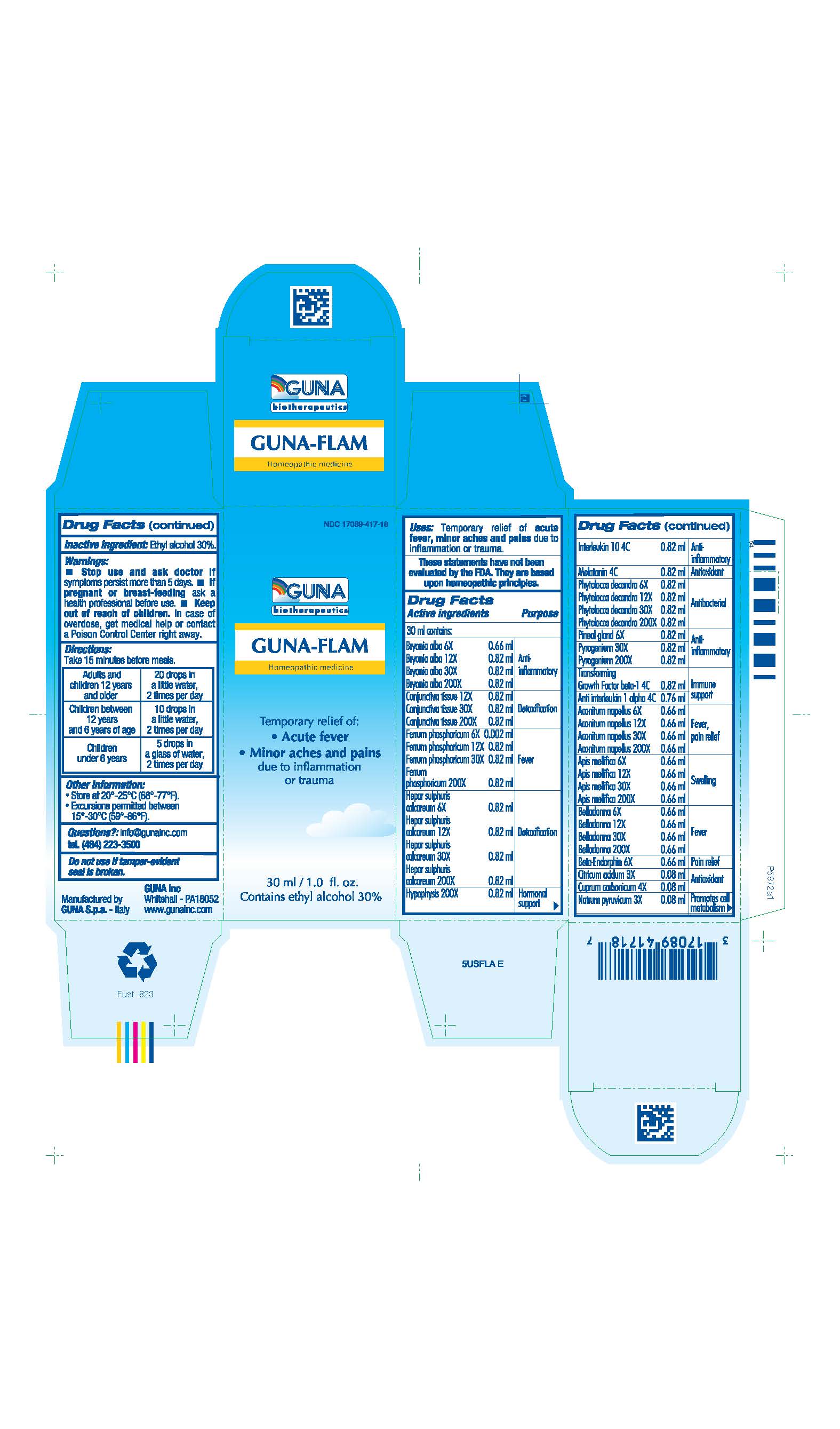 DRUG LABEL: GUNA-FLAM
NDC: 17089-417 | Form: SOLUTION/ DROPS
Manufacturer: Guna spa
Category: homeopathic | Type: HUMAN OTC DRUG LABEL
Date: 20200615

ACTIVE INGREDIENTS: ACONITUM NAPELLUS 6 [hp_X]/30 mL; ANTI-INTERLEUKIN-1.ALPHA. IMMUNOGLOBULIN G RABBIT 4 [hp_C]/30 mL; APIS MELLIFERA 6 [hp_X]/30 mL; ATROPA BELLADONNA 6 [hp_X]/30 mL; METENKEFALIN 6 [hp_X]/30 mL; BRYONIA ALBA ROOT 6 [hp_X]/30 mL; CITRIC ACID MONOHYDRATE 3 [hp_X]/30 mL; SUS SCROFA CONJUNCTIVA 12 [hp_X]/30 mL; BASIC CUPRIC CARBONATE 4 [hp_X]/30 mL; FERRIC PHOSPHATE 6 [hp_X]/30 mL; CALCIUM SULFIDE 6 [hp_X]/30 mL; SUS SCROFA PITUITARY GLAND 200 [hp_X]/30 mL; INTERLEUKIN-10 4 [hp_C]/30 mL; MELATONIN 4 [hp_C]/30 mL; SODIUM PYRUVATE 3 [hp_X]/30 mL; PHYTOLACCA AMERICANA ROOT 6 [hp_X]/30 mL; SUS SCROFA PINEAL GLAND 6 [hp_X]/30 mL; RANCID BEEF 30 [hp_X]/30 mL; TRANSFORMING GROWTH FACTOR BETA-1 4 [hp_C]/30 mL
INACTIVE INGREDIENTS: ALCOHOL

GUNA-FLAM

ACTIVE INGREDIENTS/PURPOSE

ACONITUM NAPELLUS 6X 12X 30X 200X FEVER, PAIN RELIEF
ANTI INTERLEUKIN 1 ALPHA 4C IMMUNE SUPPORT
APIS MELLIFICA 6X 12X 30X 200X SWELLING
BELLADONNA 6X 12X 30X 200X FEVER
BETA-ENDORPHIN 6X PAIN RELIEF
BRYONIA ALBA 6X 12X 30X 200X ANTI-INFLAMMATORY
CITRICUM ACIDUM 3X ANTIOXIDANT
CONJUNCTIVA TISSUE 12X 30X 200X DETOXIFICATION
CUPRUM CARBONICUM 4X ANTIOXIDANT
FERRUM PHOSPHORICUM 6X 12X 30X 200X FEVER
HEPAR SULFURIS CALCAREUM 6X 12X 30X 200X DETOXIFICATION
HYPOPHYSIS 200X HORMONAL SUPPORT
INTERLEUKIN 10 4C ANTI-INFLAMMATORY
MELATONIN 4C ANTIOXIDANT
NATRUM PYRUVICUM 3X PROMOTES CELL METABOLISM
PHYTOLACCA DECANDRA 6X 12X 30X 200X ANTIBACTERIAL
PINEAL GLAND 6X ANTI-INFLAMMATORY
PYROGENIUM 30X 200X ANTI-INFLAMMATORY
TRANSFORMING GROWTH FACTOR BETA-1 4C IMMUNE SUPPORT

DOSAGE AND ADMINISTRATION

Adults and children twelve years and older: 20 drops in a little water, 2 times per day

Children between 12 years and 6 years of age: 10 drops in a little water, 2 times per day

Children under 6 years: 5 drops in a glass of water, 2 times per day

WARNINGS

- Stop use and ask doctor if symptoms persist more than 5 days.
- If pregnant or breast-feeding ask a health professional before use.
- Keep out of reach of children. In case of overdose, get medical help or contact a Poison Control Center right away.
- Contains ethyl alcohol 30%

PREGNANCY

If pregnant or breast-feeding ask a doctor before use

WARNINGS

Keep this and all medicines out of reach of children

DIRECTIONS

Take 15 minutes before meals

QUESTIONS

Questions?: info@gunainc.com, tel. (484) 223-3500

PURPOSE

Temporary relief of:

- Acute Fever
- Minor Aches and pains due to inflammation or trauma

Inactive Ingredient: Ethyl alcohol 30%.